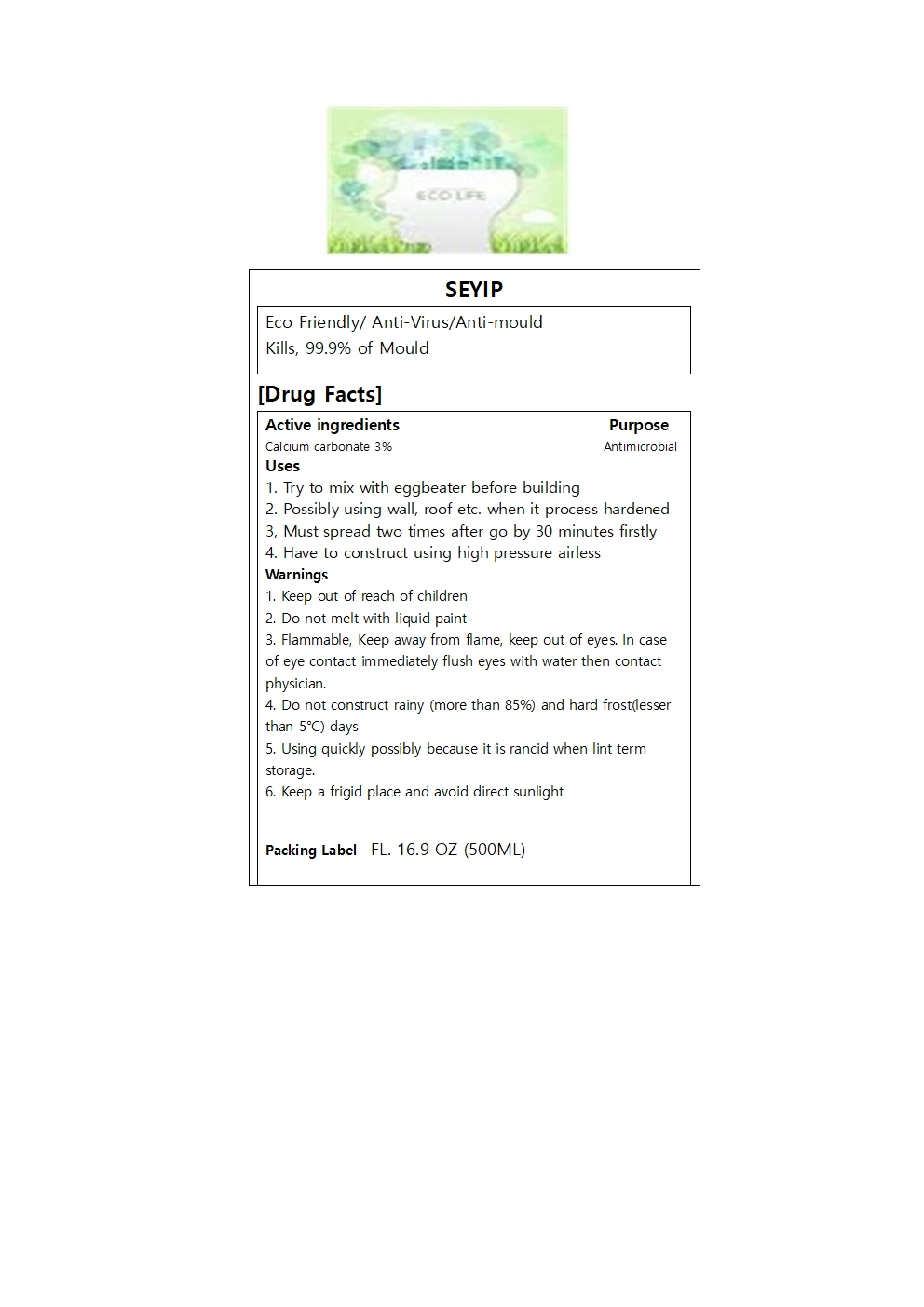 DRUG LABEL: SEYIP
NDC: 82585-303 | Form: LIQUID
Manufacturer: seaip co., Ltd
Category: otc | Type: HUMAN OTC DRUG LABEL
Date: 20220413

ACTIVE INGREDIENTS: CALCIUM CARBONATE 3 mg/100 mL
INACTIVE INGREDIENTS: DIATOMACEOUS EARTH; WATER; POLYQUATERNIUM-10 (1000 MPA.S AT 2%); ALUMINUM SILICATE; SODIUM ALGINATE; KAOLIN; SODIUM BIS(1,3-DIMETHYLBUTYL) SULFOSUCCINATE; 4-METHYL-1-PENTANOL; CALCIUM HYDROXIDE; ZEOLITE A

Active Ingredient

calcium carbonate

Purpose

Antimicrobial

Use

1. Try to mix with eggbeater before building

2. Possibly using wall, roof etc. when it process hardened

Use

3. Must spread two times after go by 30 minutes firstly

4. Have to construct using high pressure airless

Warnings

Do not melt with liquid paint

Do not construct rainy(more than 85%) and hard frost(lesser than 5°C) days

Using quickly possibly because it is rancid when long term storage

Keep a frigid place and avoid direct sunlight

Warnings

Flammable, Keep away from flame, keep out of eyes. In case of eye contact immediately flush eyes with water then contact physician.

Warnings

Keep out of reach of children

Inactive Ingredient

POLYQUATERNIUM-10 (1000 MPA.S AT 2%)

4-METHYL-1-PENTANOL

CALCIUM HYDROXIDE

ZEOLITE A

WATER

ALUMINUM SILICATE

SODIUM ALGINATE

KAOLIN

SODIUM BIS(1,3-DIMETHYLBUTYL) SULFOSUCCINATE

DIATOMACEOUS EARTH

Package Label

syeip image